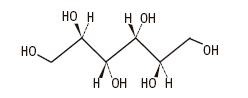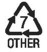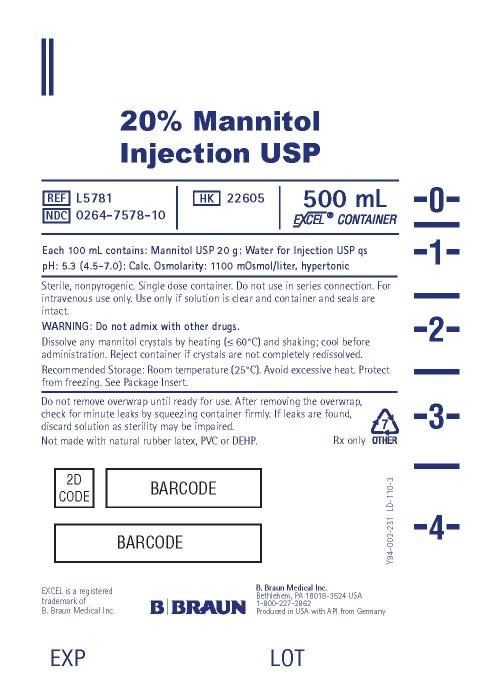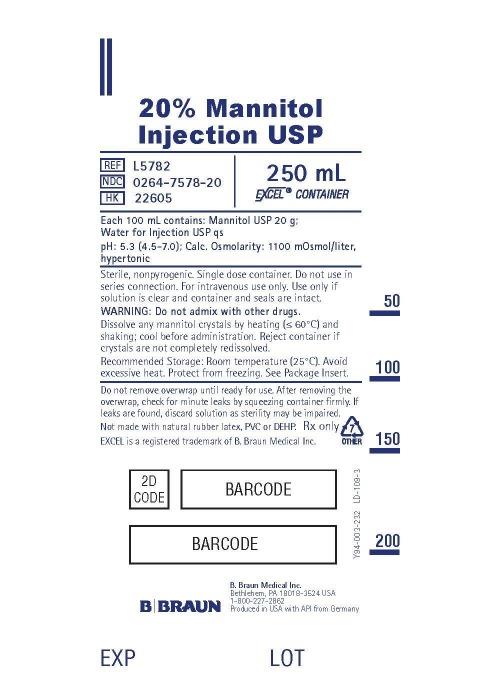 DRUG LABEL: Mannitol
NDC: 0264-7578 | Form: INJECTION, SOLUTION
Manufacturer: B. Braun Medical Inc.
Category: prescription | Type: HUMAN PRESCRIPTION DRUG LABEL
Date: 20230815

ACTIVE INGREDIENTS: MANNITOL 20 g/100 mL
INACTIVE INGREDIENTS: WATER

HIGHLIGHTS OF PRESCRIBING INFORMATION

These highlights do not include all the information needed to use MANNITOL INJECTION safely and effectively. See full prescribing information for MANNITOL INJECTION.
MANNITOL Injection, for intravenous use
Initial U.S. Approval: 1964

RECENT MAJOR CHANGES

Indications and Usage (removed, revised) (1) 09/2019
Contraindications (4) 09/2019
Warnings and Precautions (5.1, 5.3, 5.7) 09/2019

1 INDICATIONS AND USAGE

Mannitol Injection is an osmotic diuretic, indicated for the reduction of:

• intracranial pressure and treatment of cerebral edema.

• elevated intraocular pressure.

2 DOSAGE AND ADMINISTRATION

Administration Instructions (2.1):

- For intravenous infusion preferably into a large central vein.
- Prior to administration, evaluate renal, cardiac and pulmonary status, and correct fluid and electrolyte imbalances.

Recommended Dosage (2.2):

- The dosage, concentration and rate of administration depend on the age, weight and condition of the patient, including fluid requirement, urinary output and concomitant therapy.
- Reduction of Intracranial Pressure: 0.25 gram/kg administered every 6 to 8 hours as an intravenous infusion over 30 minutes.
- Reduction of Intraocular Pressure: 1.5 to 2 grams/kg of a 15% or 20% w/v solution as a single dose administered intravenously over at least 30 minutes.

3 DOSAGE FORMS AND STRENGTHS

Injection: 20% (0.2 grams/mL): 20 grams of mannitol, USP per 100 mL in single-dose 250 mL and 500 mL flexible containers.

4 CONTRAINDICATIONS

- Known hypersensitivity to mannitol. (4, 5.1)
- Anuria. (4, 5.2)
- Severe hypovolemia. (4, 5.4)
- Pre-existing severe pulmonary vascular congestion or pulmonary edema. (4, 5.5)
- Active intracranial bleeding except during craniotomy. (4)

5 WARNINGS AND PRECAUTIONS

- Hypersensitivity Reactions, including anaphylaxis: Stop infusion immediately if hypersensitivity reactions develop. (5.1)
- Renal Complications Including Renal Failure: Risk factors include preexisting renal failure, concomitant use of nephrotoxic drugs or
  other diuretics. Avoid use of nephrotoxic drugs. Discontinue Mannitol Injection if renal function worsens. (5.2, 8.6)
- Central Nervous System (CNS) Toxicity: Confusion, lethargy and coma may occur during or after infusion. Concomitant neurotoxic drugs may potentiate toxicity. Avoid use of neurotoxic drugs. Discontinue Mannitol Injection if CNS toxicity develops. (5.3)
- Fluid and Electrolyte Imbalances, Hyperosmolarity: Hypervolemia may exacerbate congestive heart failure, hyponatremia can lead to encephalopathy; hypo/hyperkalemia can result in cardiac adverse reactions in sensitive patients. Discontinue Mannitol Injection if fluid and/or electrolyte imbalances occur. (5.4)
- Monitoring/Laboratory Tests: Monitor fluid and electrolytes, serum osmolarity and renal, cardiac and pulmonary function. Discontinue if toxicity develops. (5.5)
- Infusion Site Reactions: May include irritation and inflammation, as well as severe reactions (compartment syndrome) when associated with extravasation. (5.6)
- Interference with Laboratory Tests: High concentrations of mannitol may cause false low results of inorganic phosphorus blood concentrations. Mannitol may produce false positive results for blood ethylene glycol. (5.7, 7.6)

6 ADVERSE REACTIONS

The most common adverse reactions are hypersensitivity reactions, renal failure, CNS toxicity, hypo/hypervolemia, hypo/hypernatremia, hypo/hyperkalemia, and infusion site reactions.

To report SUSPECTED ADVERSE REACTIONS, contact B. Braun Medical Inc. at 1-800-854-6851 or FDA at 1-800-FDA-1088 or www.fda.gov/medwatch.

7 DRUG INTERACTIONS

- Nephrotoxic Drugs and Diuretics: May increase the risk of renal failure; avoid concomitant use. (7.1, 7.2)
- Neurotoxic Drugs: May potentiate CNS toxicity of mannitol; avoid concomitant use. (7.3)
- Drugs Affected by Electrolyte Imbalances: May result in cardiac adverse reactions; monitor serum electrolytes and discontinue Mannitol Injection if cardiac status worsens. (7.4)
- Renally Eliminated Agents: Concomitant use may decrease the effectiveness of agents that undergo significant renal elimination. However, concomitant use of mannitol and lithium may increase risk of lithium toxicity. If concomitant use is necessary, frequently monitor lithium concentrations and for signs of toxicity. (7.5)

FULL PRESCRIBING INFORMATION

1 INDICATIONS AND USAGE

Mannitol Injection is indicated for:

- Reduction of intracranial pressure and treatment of cerebral edema.
- Reduction of elevated intraocular pressure.

2 DOSAGE AND ADMINISTRATION

2.1 Important Preparation and Administration Instructions

- Mannitol Injection is for intravenous use only, preferably into a large central vein [see Warnings and Precautions (5.6), Description (11)].
- Prior to administration of Mannitol Injection, evaluate renal, cardiac and pulmonary status of the patient and correct fluid and electrolyte imbalances [see Dosage and Administration (2.2)].
- Do not administer Mannitol Injection simultaneously with blood products through the same administration set because of the possibility of pseudoagglutination or hemolysis. If it is essential that blood be given simultaneously, at least 20 mEq of sodium chloride should be added to each liter of mannitol solution to avoid pseudoagglutination.

Preparation

1. Tear overwrap and remove solution container.
2. Visually inspect the container. The closure system has two ports; the one for the administration set has a tamper evident plastic protector and the other is a medication addition site. Use only if solution is clear and container and seals are intact.
  - Check for minute leaks by squeezing inner bag firmly. If leaks are found, discard solution as sterility may be impaired.
  - Invert container and carefully inspect the solution in good light for cloudiness, haze, or particulate matter. Any container which is suspect should not be used.
3. Admixing Mannitol Injection with other medications is not recommended. The addition of sodium chloride to 20% mannitol solution may result in precipitation of mannitol.
4. Inspect Mannitol Injection visually for particulate matter and discoloration prior to administration and periodically during administration. If particulates or discoloration are present, discard the bag.
5. Solutions of mannitol may crystallize when exposed to low temperatures. Concentrations greater than 15% have a greater tendency to crystallization. Inspect for crystals prior to administration. If crystals are observed, the container should be warmed by appropriate means to not greater than 60°C, shaken, then cooled to body temperature before administering. If all crystals cannot be completely redissolved, the container must be discarded.

Administration

1. Administer intravenously using sterile, filter-type administration set. It is recommended that Mannitol Injection be administered through a blood filter set to ensure against infusion of mannitol crystals.
2. When administered peripherally, infuse slowly through a small bore needle, placed well within the lumen of a large vein to minimize venous irritation. Carefully avoid infiltration.
3. Do not admix with other drugs. The use of supplemental additive medication is not recommended.
4. To prevent air embolism, use a non-vented infusion set or close the vent on a vented set, avoid multiple connections, do not connect flexible containers in series, fully evacuate residual gas in the container prior to administration, do not pressurize the flexible container to increase flow rates, and if administration is controlled by a pumping device, turn off pump before the container runs dry.
5. For single use only; discard unused portion.

2.2 Recommended Dosage

Prior to administration of Mannitol Injection, evaluate renal, cardiac and pulmonary status of the patient and correct fluid and electrolyte imbalances.

The total dosage, concentration, and rate of administration depend on the age, weight, and condition of the patient being treated, including fluid requirement, electrolyte balance, serum osmolality, urinary output, and concomitant therapy.

The following outline of administration and dosage is only a general guide to therapy.

Reduction of Intracranial Pressure
Usually a maximum reduction in intracranial pressure in adults can be achieved with a dose of 0.25 g/kg infused intravenously over 30 minutes, which may be repeated every six to eight hours.

During and following Mannitol Injection infusion, monitor fluid and electrolytes, serum osmolarity, and renal, cardiac and pulmonary function. Discontinue Mannitol Injection if renal, cardiac, or pulmonary status worsens or CNS toxicity develops [see Warnings and Precautions (5.2, 5.3, 5.4, 5.5)].

Reduction of Intraocular Pressure
The recommended dosage is 1.5 to 2 g/kg of a 20% solution (7.5 to 10 mL/kg) as a single dose infused intravenously over a period of at least 30 minutes. When used preoperatively, administer one to one and one-half hours before surgery to achieve maximal reduction of intraocular pressure before operation.

3 DOSAGE FORMS AND STRENGTHS

Mannitol Injection 20%, USP is a clear and colorless solution of 20 grams of mannitol, USP per 100 mL (0.2 grams/mL) in single-dose 250 mL and 500 mL flexible containers.

4 CONTRAINDICATIONS

Mannitol Injection is contraindicated in patients with:

- Hypersensitivity to mannitol [see Warnings and Precautions (5.1)]
- Anuria [see Warnings and Precautions (5.2)]
- Severe hypovolemia [see Warnings and Precautions (5.4)]
- Pre-existing severe pulmonary vascular congestion or pulmonary edema [see Warnings and Precautions (5.5)]
- Active intracranial bleeding except during craniotomy.

5 WARNINGS AND PRECAUTIONS

5.1 Hypersensitivity Reactions

Serious hypersensitivity reactions, including anaphylaxis, hypotension and dyspnea resulting in cardiac arrest and death have been reported with Mannitol Injection [see Adverse Reactions (6)]. Stop the infusion immediately if signs or symptoms of a suspected hypersensitivity reaction develop. Initiate appropriate therapeutic countermeasures as clinically indicated.

5.2 Renal Complications Including Renal Failure

Renal complications, including irreversible renal failure have been reported in patients receiving mannitol.

Reversible, oliguric acute kidney injury (AKI) has occurred in patients with normal pretreatment renal function who received large intravenous doses of mannitol.

Although the osmotic nephrosis associated with mannitol administration is in principle reversible, osmotic nephrosis in general is known to potentially proceed to chronic or even end-stage renal failure. Monitor renal function closely during infusion of Mannitol Injection. Patients with pre-existing renal disease, patients with conditions that put them at high risk for renal failure, or those receiving potentially nephrotoxic drugs or other diuretics, are at increased risk of renal failure following administration of Mannitol Injection. Avoid concomitant administration of nephrotoxic drugs (e.g., aminoglycosides) or, other diuretics with Mannitol Injection, if possible [see Drug Interactions (7.1, 7.2)].

Patients with oliguric AKI who subsequently develop anuria while receiving mannitol are at risk of congestive heart failure, pulmonary edema, hypertensive crisis, coma and death.

During and following Mannitol Injection infusion for reduction in intracranial pressure, monitor the patient clinically and review laboratory tests for changes in fluid and electrolyte status. Discontinue Mannitol Injection if renal function worsens [see Warnings and Precautions (5.5)].

5.3 Central Nervous System (CNS) Toxicity

CNS toxicity manifested by, e.g., confusion, lethargy, or coma has been reported in patients treated with mannitol, with fatal outcomes identified, in particular in the presence of impaired renal function CNS toxicity may result from high serum mannitol concentrations, serum hyperosmolarity resulting in intracellular dehydration within CNS, hyponatremia or other disturbances of electrolyte and acid/base balance secondary to mannitol administration [see Warnings and Precautions (5.4)].

At high concentrations, mannitol may cross the blood brain barrier and interfere with the ability of the brain to maintain the pH of the cerebrospinal fluid especially in the presence of acidosis.

In patients with preexisting compromise of the blood brain barrier, the risk of increasing cerebral edema (general and focal) associated with repeated or continued use of 20% Mannitol Injection USP must be individually weighed against the expected benefits.

A rebound increase of intracranial pressure may occur several hours after the infusion. Patients with a compromised blood brain barrier are at increased risk.

Concomitant administration of nephrotoxic drugs (e.g., aminoglycosides) with Mannitol Injection may potentiate neurotoxicity. Avoid concomitant use of neurotoxic drugs, if possible [see Drug Interactions (7.3)].

During and following infusion of Mannitol Injection for the reduction in intracranial pressure, monitor the patient clinically and laboratory tests for changes in fluid and electrolyte status. Discontinue Mannitol Injection if CNS toxicity develops. [see Warnings and Precautions (5.5)].

5.4 Fluid and Electrolyte Imbalances, Hyperosmolarity

Depending on dosage and duration, administration of Mannitol Injection may result in hypervolemia leading to or exacerbating existing congestive heart failure. Accumulation of mannitol due to insufficient renal excretion increases the risk of hypervolemia.

Mannitol-induced osmotic diuresis may cause or worsen dehydration/hypovolemia and hemoconcentration. Administration of Mannitol Injection may also cause hyperosmolarity [see Description (11)].

The obligatory diuretic response following rapid infusion of Mannitol Injection may further aggravate preexisting hemoconcentration. Excessive loss of water and electrolytes may lead to serious imbalances. Serum sodium and potassium should be carefully monitored during mannitol administration.

Depending on dosage and duration of administration, electrolyte and acid/base imbalances may also result from transcellular shifts in water and electrolytes, osmotic diuresis and/or other mechanisms. Such imbalances may be severe and potentially fatal.

Imbalances that may result from Mannitol Injection administration include:

• Hypernatremia, dehydration and hemoconcentration

• Hyponatremia, which can lead to headache, nausea, seizures, lethargy, coma, cerebral edema, and death. Acute symptomatic hyponatremic encephalopathy is considered a medical emergency.

• Hypo/hyperkalemia. The development of electrolyte imbalances (e.g., hyperkalemia, hypokalemia) associated with mannitol administration may result in cardiac adverse reactions in patients receiving drugs that are sensitive to such imbalances (e.g., digoxin, agents that may cause QT prolongation, neuromuscular blocking agents) [see Drug Interactions (7.4)].

• Other electrolyte disturbances

• Metabolic acidosis/alkalosis

Pediatric patients less than two years of age, particularly preterm and term neonates, may be at higher risk for fluid and electrolyte abnormalities following Mannitol Injection administration due to decreased glomerular filtration rate and limited ability to concentrate urine [see Use in Specific Populations (8.4)]

During and following Mannitol Injection infusion for the reduction in intracranial pressure, monitor fluid, acid-base balance and electrolyte status and discontinue Mannitol Injection if imbalances occur [see Warnings and Precautions (5.5)].

5.5 Monitoring/Laboratory Tests

During and following infusion of Mannitol Injection for the reduction in intracranial pressure, monitor:

• serum osmolarity, serum electrolytes (including sodium, potassium, calcium and phosphate) and acid base balance

• the osmol gap

• signs of hypo- or hypervolemia, including urine output

• renal, cardiac and pulmonary function

• intracranial pressure

Discontinue Mannitol Injection if renal, cardiac, or pulmonary status worsens, or CNS toxicity develops [see Contraindications (4)].

5.6 Infusion Site Reactions

The infusion of hypertonic solutions through a peripheral vein, including Mannitol Injection, may result in peripheral venous irritation, including phlebitis. Other severe infusion site reactions, such as compartment syndrome and swelling associated with extravasation, can occur with administration of Mannitol Injection [see Adverse Reactions (6)]. Mannitol Injection is preferably for administration into a large central vein [see Dosage and Administration (2.1)].

5.7 Interference with Laboratory Tests

High concentrations of mannitol can cause false low results for inorganic phosphorus blood concentrations [see Drug Interactions (7.6)].

Mannitol may produce false positive results in tests for blood ethylene glycol concentrations [see Drug Interactions (7.6)].

6 ADVERSE REACTIONS

The following adverse reactions from voluntary reports or clinical studies have been reported with mannitol injection. Because many of these reactions were reported voluntarily from a population of uncertain size, it is not always possible to reliably estimate their frequency or establish a causal relationship to drug exposure.

• Hypersensitivity Reactions: cardiac arrest, anaphylaxis, hypotension, dyspnea, hypertension, pyrexia, chills, sweating, cough, musculoskeletal stiffness, myalgia, urticarial/rash, pruritus, generalized pain, discomfort, nausea, vomiting, and headache [see Warnings and Precautions (5.1)]

• Renal Failure: acute kidney injury, osmotic nephrosis, azotemia, anuria, hematuria, oliguria, polyuria [see Warnings and Precautions (5.2)]

• CNS Toxicity: headache, coma, seizures, confusion, lethargy; rebound increase in intracranial pressure; dizziness [see Warnings and Precautions (5.3)]

• Fluid and Electrolyte Imbalances: hypovolemia, hypervolemia, peripheral edema, dehydration, hyponatremia, hypernatremia, hyperkalemia, hypokalemia; metabolic acidosis [see Warnings and Precautions (5.4)]

• Infusion Site Reactions: infection, venous thrombosis or phlebitis, inflammation, pain, rash, erythema, pruritus, compartment syndrome and swelling associated with extravasation [see Warnings and Precautions (5.6)]

• Cardiac and Respiratory Disorders: rhinitis, congestive cardiac failure, pulmonary edema, palpitations, hypotension, hypertension, tachycardia, and angina-like chest pains.

• Gastrointestinal Disorders: thirst, dry mouth, nausea, vomiting

• Other: asthenia, malaise, fever, chills, urticaria

7 DRUG INTERACTIONS

7.1 Nephrotoxic Drugs

Concomitant administration of nephrotoxic drugs (e.g., cyclosporine, aminoglycosides) increases the risk of renal failure following administration of mannitol. Avoid use of nephrotoxic drugs with Mannitol Injection, if possible [see Warnings and Precautions (5.2)].

7.2 Diuretics

Concomitant administration of other diuretics may potentiate the renal toxicity of mannitol. Avoid use of other diuretics with Mannitol Injection, if possible [see Warnings and Precautions (5.2)].

7.3 Neurotoxic Drugs

Concomitant administration of systemic neurotoxic drugs (e.g., aminoglycosides) with Mannitol Injection may potentiate the CNS toxicity of mannitol. Avoid use of systemic neurotoxic drugs with Mannitol Injection, if possible [see Warnings and Precautions (5.3)].

7.4 Drugs Affected by Electrolyte Imbalances

The development of electrolyte imbalances (e.g., hyperkalemia, hypokalemia) associated with mannitol administration may result in cardiac adverse reactions in patients receiving drugs that are sensitive to such imbalances (e.g., digoxin, drugs that prolong the QT interval, neuromuscular blocking agents) [see Warnings and Precautions (5.4)]. During and following infusion of Mannitol Injection, monitor serum electrolytes and discontinue Mannitol Injection if cardiac status worsens [see Warnings and Precautions (5.5)].

7.5 Renally Eliminated Drugs

Mannitol therapy may increase the elimination and decrease the effectiveness of treatment with drugs that undergo significant renal elimination. Concomitant administration of mannitol with lithium may initially increase the elimination of lithium but may also increase the risk of lithium toxicity if patients develop hypovolemia or renal impairment. In patients receiving lithium, consider holding lithium doses during treatment with Mannitol Injection. In patients requiring concomitant administration of lithium and Mannitol Injection, frequently monitor serum lithium concentrations and for signs of lithium toxicity.

7.6 Interference with Laboratory Tests

High concentrations of mannitol can cause false low results for inorganic phosphorus blood concentrations when an assay based on the conversion of phosphate (orthophosphate) to the phosphomolybdate complex is used.
Mannitol may produce false positive results in tests for blood ethylene glycol concentrations in which mannitol is initially oxidized to an aldehyde.

8 USE IN SPECIFIC POPULATIONS

8.1 Pregnancy

Risk Summary

The available case report data with mannitol over decades of use have not identified a drug-associated risk of major birth defects, miscarriage or adverse maternal or fetal outcomes. Mannitol crosses the placenta and may cause fluid shifts that could potentially result in adverse effects in the fetus (see Data). No adverse developmental effects from mannitol were reported in published animal studies; however, fluid shifts occurred in fetal ewes in response to maternal infusion of mannitol.

The estimated background risk of major birth defects and miscarriage for the indicated population is unknown. All pregnancies have a background risk of birth defect, loss, or other adverse outcomes. In the U.S. general population, the estimated background risk of major birth defects and miscarriage in clinically recognized pregnancies is 2 to 4% and 15 to 20%, respectively.

Data

Human Data

Published literature reports the presence of mannitol in amniotic fluid when mannitol is administered to pregnant women during the third trimester of pregnancy.

8.2 Lactation

Risk Summary

There are no data on the presence of mannitol in either human or animal milk, the effects of on the breastfed infant, or the effects on milk production. The developmental and health benefits of breastfeeding should be considered along with the mother’s clinical need for Mannitol Injection and any potential adverse effects on the breastfed infant from Mannitol Injection or from the underlying maternal condition.

8.4 Pediatric Use

Mannitol Injection is approved for use in the pediatric population for the reduction of intracranial and intraocular pressure. Studies have not defined the optimal dose of Mannitol Injection in the pediatric population. The safety profile for mannitol use in pediatric patients is similar to adults at dosages described in labeling. However, pediatric patients less than two years of age, particularly preterm and term neonates, may be at higher risk for fluid and electrolyte abnormalities following Mannitol Injection administration due to decreased glomerular filtration rate and limited ability to concentrate urine [see Warnings and Precautions (5.4)].

8.5 Geriatric Use

Mannitol is known to be substantially excreted by the kidney and the risk of adverse reactions to this drug may be greater in elderly patients with impaired renal function. Evaluate the renal, cardiac and pulmonary status of the patient and correct fluid and electrolyte imbalances prior to administration of Mannitol Injection [see Warnings and Precautions (5.2, 5.3, 5.4, 5.5)].

8.6 Renal Impairment

Patients with pre-existing renal disease, patients with conditions that put them at risk for renal failure, or those receiving potentially nephrotoxic drugs or other diuretics, are at increased risk of renal failure with administration of mannitol. Evaluate the renal, cardiac and pulmonary status of the patient and correct fluid and electrolyte imbalances prior to administration of Mannitol Injection [see Warnings and Precautions (5.2, 5.3, 5.4, 5.5)].

10 OVERDOSAGE

Signs and symptoms of overdose with Mannitol Injection include renal failure and acute kidney injury, hypo/hypervolemia, hyperosmolarity and electrolyte imbalances, CNS toxicity (e.g., coma, seizures), some of which can be fatal [see Warnings and Precautions (5.2, 5.3, 5.4)].

Management of overdosage with Mannitol Injection is symptomatic and supportive. Discontinue the infusion and institute appropriate corrective measures with particular attention to renal, cardiac and pulmonary systems. Correct fluid and electrolyte imbalances.

Mannitol Injection is dialyzable (hemodialysis and peritoneal dialysis): dialysis may increase Mannitol Injection elimination.

11 DESCRIPTION

Mannitol Injection 20%, USP is a sterile, nonpyrogenic solution of Mannitol, USP in 250 mL and 500 mL single-dose EXCEL® flexible containers for intravenous administration as an osmotic diuretic. It contains no antimicrobial agents. Mannitol is a six-carbon sugar alcohol prepared commercially by the reduction of dextrose.

Each 100 mL contains:

Mannitol USP 20 g; Water for Injection USP qs

pH: 5.3 (4.5-7.0); Calculated Osmolarity 1100 mOsmol/liter

Normal physiologic osmolarity range is approximately 280 to 310 mOsmol/L.

The formula of the active ingredient is:

Ingredient | Molecular Formula | Molecular Weight
Mannitol USP |  | 182.17

The EXCEL® plastic container is made from a multilayered film specifically developed for parenteral drugs. It contains no plasticizers. The solution contact layer is a rubberized copolymer of ethylene and propylene. Solutions in contact with the plastic container may leach out certain chemical components from the plastic in very small amounts; however, biological testing was supportive of the safety of the plastic container materials. The container-solution unit is a closed system and is not dependent upon entry of external air during administration. The container is overwrapped to provide protection from the physical environment and to provide an additional moisture barrier when necessary. Exposure to temperatures above 25°C/77°F during transport and storage will lead to minor losses in moisture content. Higher temperatures lead to greater losses. It is unlikely that these minor losses will lead to clinically significant changes within the expiration period.

12 CLINICAL PHARMACOLOGY

12.1 Mechanism of Action

Mannitol, when administered intravenously, exerts its osmotic effect as a solute of relatively small molecular size being largely confined to the extracellular space. Mannitol hinders tubular reabsorption of water and enhances excretion of sodium and chloride by elevating the osmolarity of the glomerular filtrate.

This increase in extracellular osmolarity effected by the intravenous administration of mannitol will induce the movement of intracellular water to the extracellular and vascular spaces. This action underlies the role of mannitol in reducing intracranial pressure, intracranial edema, and elevated intraocular pressure.

12.3 Pharmacokinetics

Distribution

Mannitol distributes largely in the extracellular space in 20 to 40 minutes after intravenous administration. The volume of distribution of mannitol is approximately 17 L in adults.

Elimination

In subjects with normal renal function, the total clearance is 87 to 109 mL/min. The elimination half-life of mannitol is 0.5 to 2.5 hours.

Metabolism

Only relatively small amount of the dose administered is metabolized after intravenous administration of mannitol to healthy subjects.

Excretion

Mannitol is eliminated primarily via the kidneys in unchanged form. Mannitol is filtered by the glomeruli, exhibits less than 10% of tubular reabsorption, and is not secreted by tubular cells. Following intravenous administration, approximately 80% of an administered dose of mannitol is estimated to be excreted in the urine in three hours with lesser amounts thereafter.

Specific Populations

Patients with Renal Impairment

In patients with renal impairment, the elimination half-life of mannitol is prolonged. In a published study, in patients with renal impairment including acute renal failure and end stage renal failure, the elimination half-life of mannitol was estimated at about 36 hours, based on serum osmolarity. In patients with renal impairment on dialysis, the elimination half-life of mannitol was reduced to 6 and 21 hours during hemodialysis and peritoneal dialysis, respectively [see Use in Specific Populations (8.6), Overdosage (10)].

16 HOW SUPPLIED/STORAGE AND HANDLING

Mannitol Injection USP, 20% (0.2 grams/mL) as a clear and colorless solution is supplied in sterile and nonpyrogenic 250 mL and 500 mL single-dose EXCEL® Containers.
Not made with natural rubber latex, PVC or DEHP.

NDC | REF | Size
0264-7578-10 | L5781 | 500 mL
0264-7578-20 | L5782 | 250 mL

The 500 mL and 250 mL containers are packaged 24 per case.

Store at room temperature (25°C).

Exposure of pharmaceutical products to heat should be minimized. Avoid excessive heat. Protect from freezing.

17 PATIENT COUNSELING INFORMATION

Inform patients or caregivers of the following risks of Mannitol Injection:

• Hypersensitivity Reactions [see Warnings and Precautions (5.1)]

• Renal Failure [see Warnings and Precautions (5.2)]

• CNS Toxicity [see Warnings and Precautions (5.3)]

• Fluid and Electrolyte Imbalances, Hyperosmolarity [see Warnings and Precautions (5.4)]

• Infusion Site Reactions [see Warnings and Precautions (5.6)]

Rx only

Manufactured by:
B. Braun Medical Inc.
Bethlehem, PA 18018-3524 USA
1-800-227-2862
Produced in USA with API from Germany

EXCEL® is a registered trademark of B. Braun Medical Inc.

Y36-002-994 LD-496-3

PRINCIPAL DISPLAY PANEL - 500 mL

20% Mannitol
Injection USP

REF L5781
NDC 0264-7578-10
HK 22605

500 mL
EXCEL® CONTAINER

Each 100 mL contains: Mannitol USP 20 g; Water for Injection USP qs
pH: 5.3 (4.5-7.0); Calc. Osmolarity: 1100 mOsmol/liter, hypertonic

Sterile, nonpyrogenic. Single dose container. Do not use in series connection. For
intravenous use only. Use only if solution is clear and container and seals are
intact.

WARNING: Do not admix with other drugs.

Dissolve any mannitol crystals by heating (< 60°C) and shaking; cool before
administration. Reject container if crystals are not completely redissolved.

Recommended Storage: Room temperature (25°C). Avoid excessive heat. Protect
from freezing. See Package Insert.

Do not remove overwrap until ready for use. After removing the overwrap,
check for minute leaks by squeezing container firmly. If leaks are found,
discard solution as sterility may be impaired.

Not made with natural rubber latex, PVC or DEHP.

Rx only

EXCEL is a registered
trademark of
B. Braun Medical Inc.

B. Braun Medical Inc.
Bethlehem, PA 18018-3524 USA
1-800-227-2862
Produced in USA with API from Germany

Y94-003-231 LD-110-3

EXP
LOT

PRINCIPAL DISPLAY PANEL - 250 mL

20% Mannitol
Injection USP

REF L5782
NDC 0264-7578-20
HK 22605

250 mL
EXCEL® CONTAINER

Each 100 mL contains: Mannitol USP 20 g;
Water for Injection USP qs

pH: 5.3 (4.5-7.0); Calc. Osmolarity: 1100 mOsmol/liter,
hypertonic

Sterile, nonpyrogenic. Single dose container. Do not use in
series connection. For intravenous use only. Use only if
solution is clear and container and seals are intact.

WARNING: Do not admix with other drugs.

Dissolve any mannitol crystals by heating (< 60°C) and
shaking; cool before administration. Reject container if
crystals are not completely redissolved.

Recommended Storage: Room temperature (25°C). Avoid
excessive heat. Protect from freezing. See Package Insert.

Do not remove overwrap until ready for use. After removing the
overwrap, check for minute leaks by squeezing container firmly. If
leaks are found, discard solution as sterility may be impaired.

Not made with natural rubber latex, PVC or DEHP.

EXCEL is a registered trademark of B. Braun Medical Inc.

Rx only

B. Braun Medical Inc.
Bethlehem, PA 18018-3524 USA
1-800-227-2862
Produced in USA with API from Germany

Y94-003-232 LD-109-3

EXP
LOT